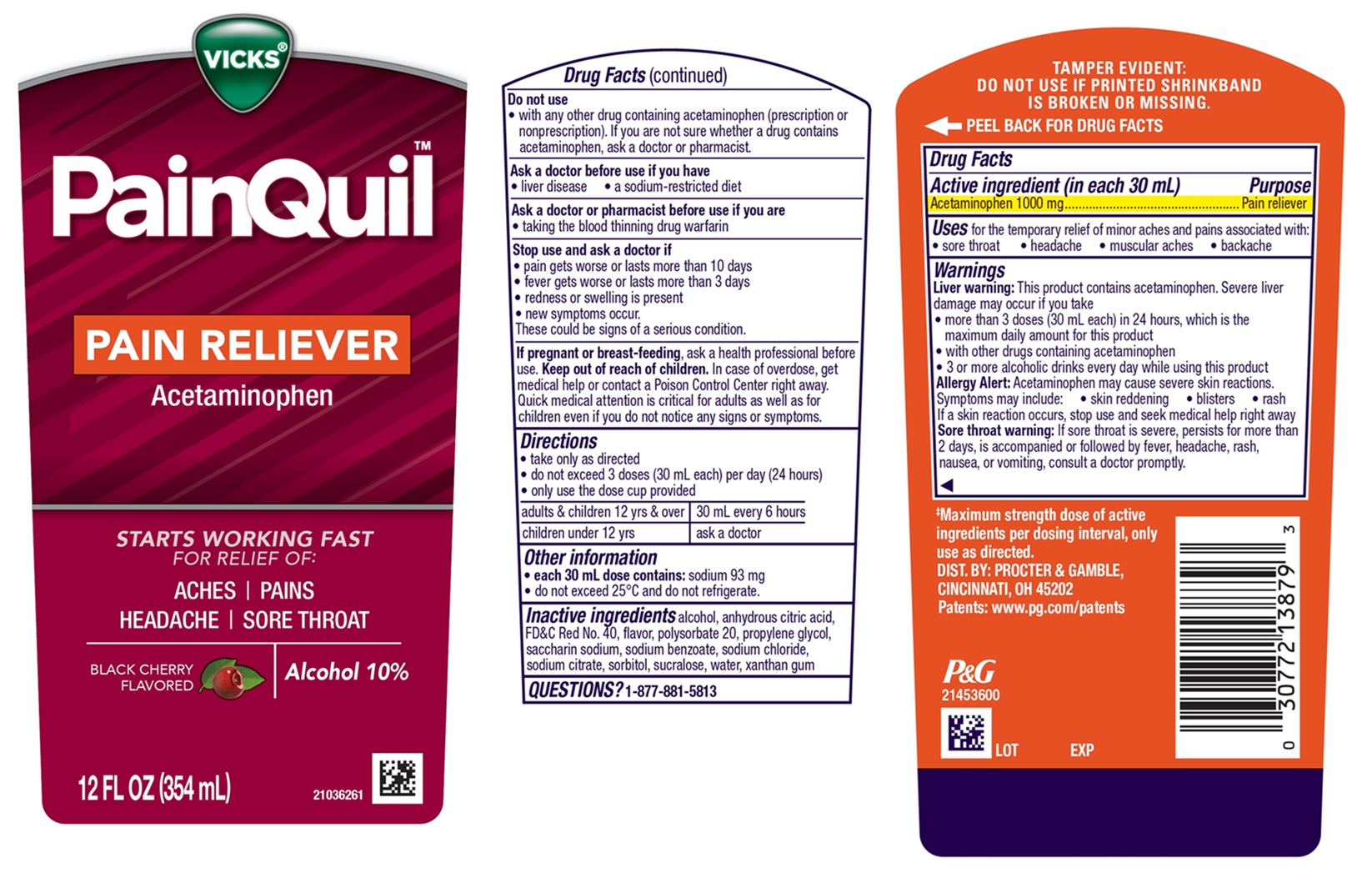 DRUG LABEL: Vicks PainQuil
NDC: 69423-833 | Form: LIQUID
Manufacturer: The Procter & Gamble Manufacturing Company
Category: otc | Type: HUMAN OTC DRUG LABEL
Date: 20251202

ACTIVE INGREDIENTS: ACETAMINOPHEN 1000 mg/30 mL
INACTIVE INGREDIENTS: PROPYLENE GLYCOL; ALCOHOL; POLYSORBATE 20; SACCHARIN SODIUM; ANHYDROUS CITRIC ACID; WATER; TRISODIUM CITRATE DIHYDRATE; FD&C RED NO. 40; SODIUM BENZOATE; SODIUM CHLORIDE; SORBITOL; SUCRALOSE; XANTHAN GUM

Vicks® PainQuil™ PAIN RELIEVER

Drug Facts

Active ingredients (in each 30 mL)

Acetaminophen 1000 mg

Purpose

Pain reliever

Uses

for the temporary relief of minor aches and pains associated with:

- sore throat
- headache
- muscular aches
- backache

Warnings

Liver warning: This product contains acetaminophen. Severe liver damage may occur if you take

- more than 3 doses (30 mL each) in 24 hours, which is the maximum daily amount for this product
- with other drugs containing acetaminophen
- 3 or more alcoholic drinks every day while using this product

Allergy Alert: Acetaminophen may cause severe skin reactions.

Symptoms may include: • skin reddening • blisters • rash

If a skin reaction occurs, stop use and seek medical help right away

Sore throat warning: If sore throat is severe, persists for more than 2 days, is accompanied or followed by fever, headache, rash, nausea, or vomiting, consult a doctor promptly.

Do not use

- with any other drug containing acetaminophen (prescription or nonprescription). If you are not sure whether a drug contains acetaminophen, ask a doctor or pharmacist.

Ask a doctor before use if you have

- liver disease
- a sodium-restricted diet

Ask a doctor or pharmacist before use if you are

- taking the blood thinning drug warfarin

Stop use and ask a doctor if

- pain gets worse or lasts more than 10 days
- fever gets worse or lasts more than 3 days
- redness or swelling is present
- new symptoms occur.

These could be signs of a serious condition.

If pregnant or breast-feeding,

ask a health professional before use.

Keep out of reach of children.

OVERDOSAGE

In case of overdose, get medical help or contact a Poison Control Center right away. Quick medical attention is critical for adults as well as for children even if you do not notice any signs or symptoms.

Directions

- take only as directed
- do not exceed 3 doses (30 mL each) per day (24 hours)
- only use the dose cup provided

adults & children 12 yrs & over | 30 mL every 6 hours
children under 12 yrs | ask a doctor

Other information

- each 30 mL contains: sodium 93 mg
- do not exceed 25°C and do not refrigerate.

Inactive ingredients

alcohol, anhydrous citric acid, FD&C Red No. 40, flavor, polysorbate 20, propylene glycol, saccharin sodium, sodium benzoate, sodium chloride, sodium citrate, sorbitol, sucralose, water, xanthan gum

QUESTIONS?

1-877-881-5813

TAMPER EVIDENT: DO NOT USE IF PRINTED SHRINKBAND IS BROKEN OR MISSING.

DIST. BY: PROCTER & GAMBLE,

CINCINNATI, OH 45202

PRINCIPAL DISPLAY PANEL - 354 ml bottle

VICKS®

PainQuil™

PAIN RELIEVER

Acetaminophen

STARTS WORKING FAST

FOR RELIEF OF:

ACHES | PAINS

HEADACHE | SORE THROAT

BLACK CHERRY FLAVORED

Alcohol 10%

12 FL OZ (354 ml)